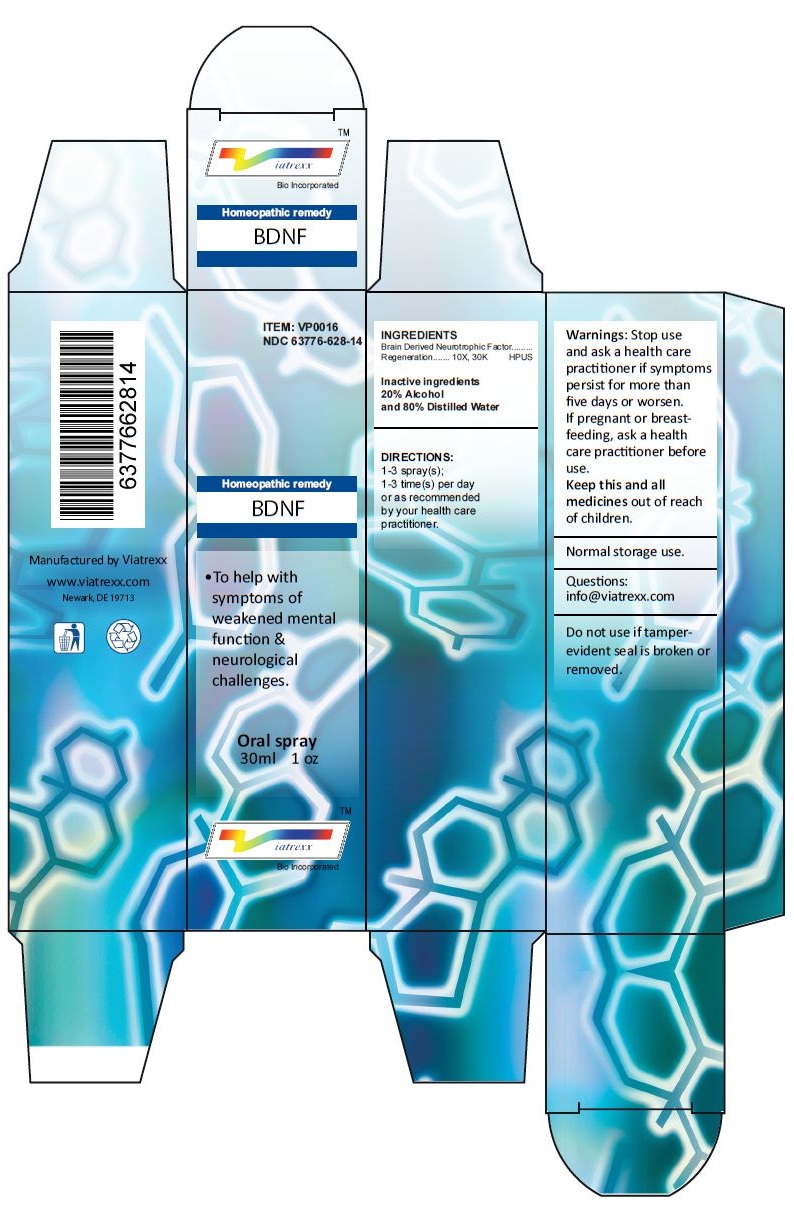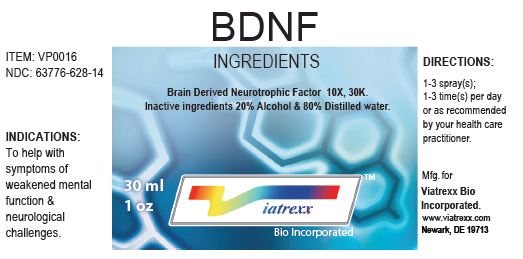 DRUG LABEL: BDNF
NDC: 63776-628 | Form: SPRAY
Manufacturer: VIATREXX BIO INCORPORATED
Category: homeopathic | Type: HUMAN OTC DRUG LABEL
Date: 20230110

ACTIVE INGREDIENTS: BRAIN-DERIVED NEUROTROPHIC FACTOR HUMAN 30 [kp_C]/1 mL
INACTIVE INGREDIENTS: ALCOHOL; WATER

BDNF

Active Ingredients

Brain Derived Neurotrophic Factor 10X, 30K

Purpose:

Brain Derived Neurotrophic Factor | Regeneration

Uses

To help with symptoms of weakened mental function & neurological challenges.

Warnings

Stop use and ask a health care practitioner if symptoms persist for more than five days or worsen. If pregnant or breastfeeding, ask a health care practitioner before use.

Dosage

1-3 spray(s); 1-3 time(s) per day or as recommended by your health care practitioner.

KEEP OUT OF REACH OF CHILDREN

Keep this and all medicines out of reach of children.

Other Ingredients

20% Alcohol and 80% Water

Other Information

Normal storage use.
Do not use if tamper-evident seal is broken or removed.

Questions

info@viatrexx.com

Principal Display Panel

ITEM: VP0016
NDC 63776-628-14
Homeopathic remedy
BDNF
• To help with symptoms of weakened mental function & neurological challenges.
Oral spray
30ml 1 oz
Viatrexx™ Bio Incorporated
Manufactured by Viatrexx
www.viatrexx.com
Newark, DE 19713

BDNF
30 ml
1 oz
Viatrexx™ Bio Incorporated
ITEM: VP0016
NDC: 63776-628-14
INDICATIONS:
To help with symptoms of weakened mental function & neurological challenges.
DIRECTIONS:
1-3 spray(s); 1-3 time(s) per day or as recommended by your health care practitioner.
Mfg. for
Viatrexx Bio Incorporated.
www.viatrexx.com
Newark, DE 19713